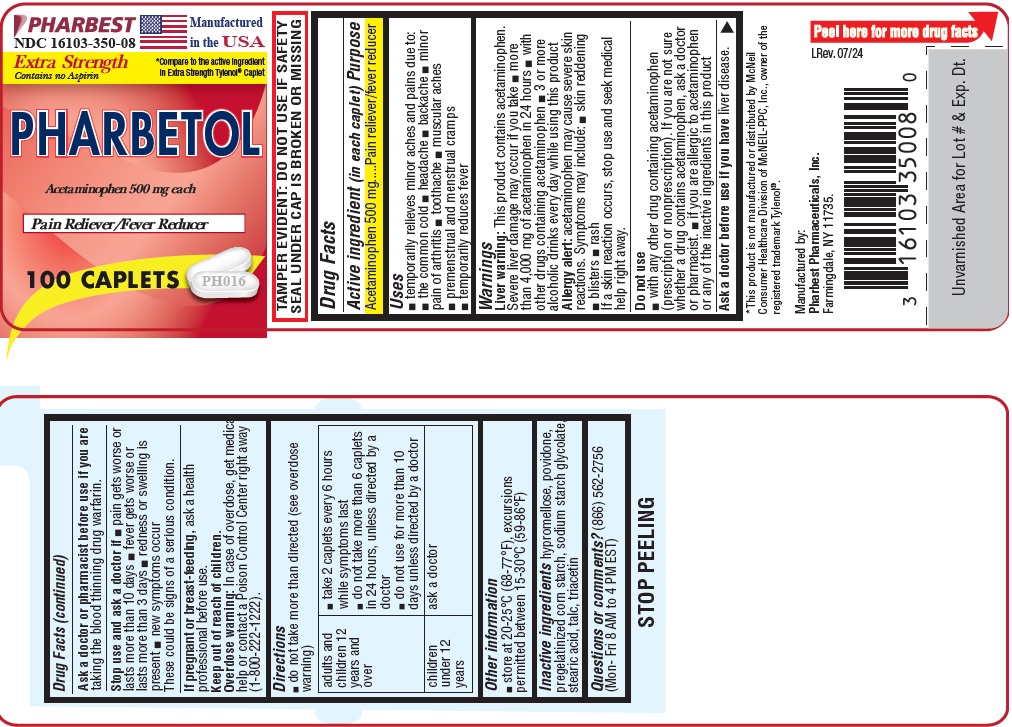 DRUG LABEL: PHARBETOL
NDC: 16103-350 | Form: TABLET, COATED
Manufacturer: Pharbest Pharmaceuticals, Inc.
Category: otc | Type: HUMAN OTC DRUG LABEL
Date: 20251224

ACTIVE INGREDIENTS: ACETAMINOPHEN 500 mg/1 1
INACTIVE INGREDIENTS: HYPROMELLOSE, UNSPECIFIED; POVIDONE, UNSPECIFIED; STARCH, CORN; SODIUM STARCH GLYCOLATE TYPE A CORN; STEARIC ACID; TALC; TRIACETIN

Drug Facts

Active ingredient (in each caplet)

Acetaminophen 500mg

Purpose

Pain Reliever/fever reducer

Uses

- temporarily relieves minor aches and pains due to:
- the common cold
- headache
- backache
- minor pain of arthritis
- toothache
- muscular aches
- premenstrual and menstrual cramps
- temporarily reduces fever

Warnings

Liver warning: This product contains acetaminophen. Severe liver damage may occur if you take

- more than 4000 mg of acetaminophen in 24 hours
- with other drugs containing acetaminophen
- 3 or more alcoholic drinks every day while using this product

Allergy alert: acetaminophen may cause severe skin reactions. Symptoms may include:

- skin reddening
- blisters
- rash

If a skin reaction occurs, stop use and seek medical help right away.

Do not use

- with any other drug containing acetaminophen (prescription or nonprescription). If you are not sure whether a drug contains acetaminophen, ask a doctor or pharmacist.

- if you are allergic to acetaminophen or any of the inactive ingredients in this product

Ask a doctor before use

if you have liver disease.

Ask a doctor or pharmacist before use if you are

taking the blood thinning drug warfarin.

Stop use and ask a doctor if

- pain gets worse or lasts more than 10 days
- fever gets worse or lasts more than 3 days
- new symptoms occur
- redness or swelling is present

These could be signs of a serious condition.

If pregnant or breast-feeding,

ask a health professional before use.

Overdose warning:

In the case of overdose, get medical help or contact a Poison Control Center right away. (1-800-222-1222).

Directions

- do not take more than directed (see overdose warning)
  adults and children 12 years and over | - take 2 caplets, every 6 hours while symptoms last - do not take more than 6 caplets in 24 hours, unless directed by a doctor - do not use more than 10 days unless directed by a doctor
  children under 12 years | ask a doctor

Other information

- Tamper Evident: do not use if imprinted safety seal under cap is broken or missing
- store at 20o-25oC (68o-77oF), excursions permitted between 15-30°C (59-86°F)

Inactive ingredients

hypromellose, povidone, pregelatinized corn starch, sodium starch glycolate, stearic acid, talc, triacetin

Questions or comments?

(866) 562-2756 (Mon - Fri 8 AM to 4 PM EST)

PACKAGE LABEL

PHARBEST

NDC 16103-350-08

Manufactured in the USA

Etra Strength

*COMPARE TO the active ingredients in Etra Strength TYLENOL® Caplet

PHARBETOL

Acetaminophen 500 mg each

Pain Reliever/Fever Reducer

THIS PACKAGE FOR HOUSEHOLD WITHOUT YOUNG CHILDREN

100 CAPLETS